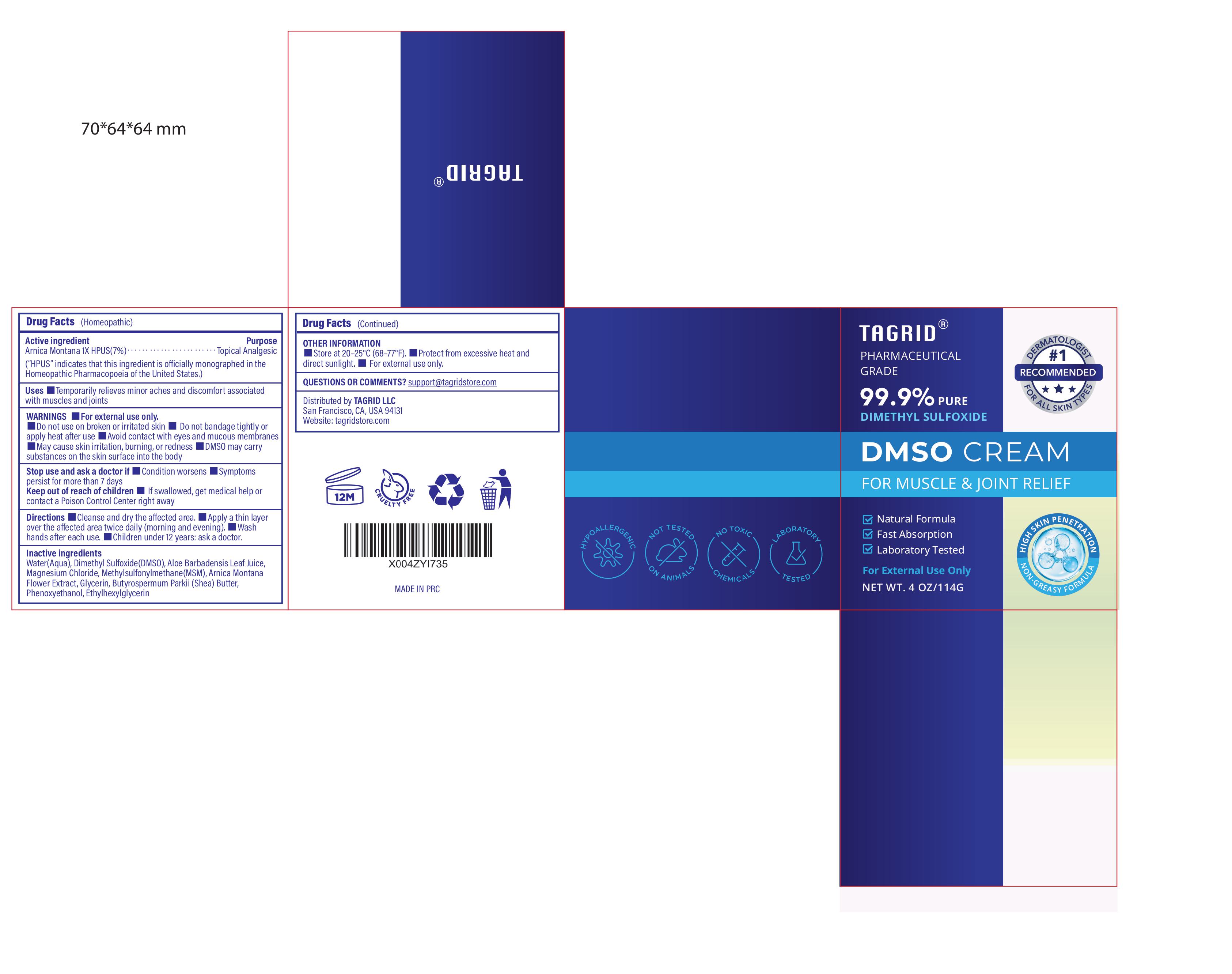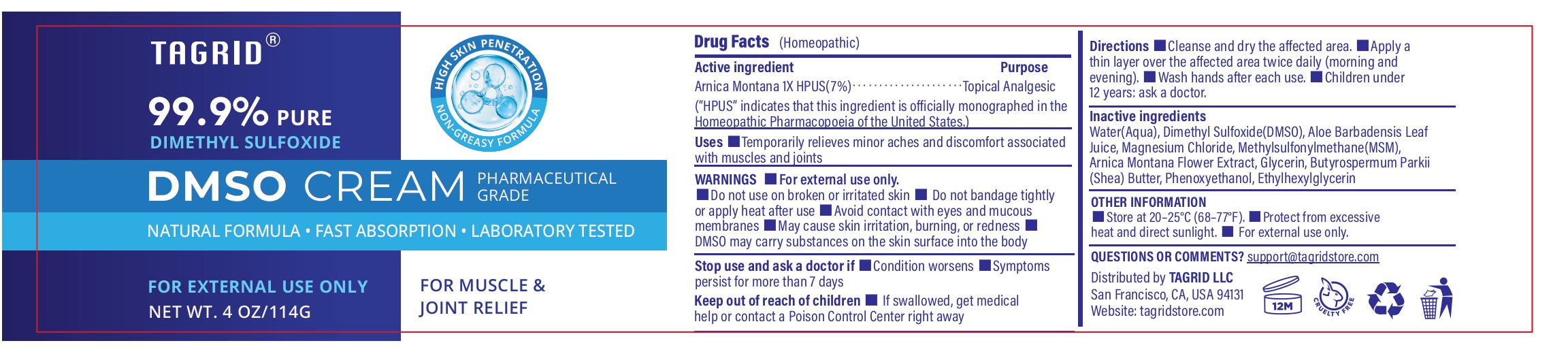 DRUG LABEL: Tagrid DMSO Cream Arnica Montana 1X HPUS (7%)
NDC: 85384-0020 | Form: CREAM
Manufacturer: TAGRID LLC
Category: homeopathic | Type: HUMAN OTC DRUG LABEL
Date: 20260215

ACTIVE INGREDIENTS: Arnica Montana 7 mg/100 g
INACTIVE INGREDIENTS: WATER; DIMETHYL SULFOXIDE; ALOE VERA LEAF JUICE; MAGNESIUM CHLORIDE; DIMETHYL SULFONE; ARNICA MONTANA FLOWER; GLYCERIN; SHEA BUTTER; PHENOXYETHANOL; ETHYLHEXYLGLYCERIN

Active ingredient:

1. Arnica Montana 1X HPUS (7%)

PURPOSE

Purpuse:Topical Analgesic.

"HPUS" indicates that this ingredient is officially monographed in the Homeopathic Pharmacopoeia of the United States

INDICATIONS AND USAGE

Uses:Temporarily relieves minor aches and discomfort associated with muscles and joints..

WARNINGS

For external use only

- Do not use on broken or irritated skin
- Do not bandage tightly or apply heat after use

When using this product

- Avoid contact with eyes and mucous membranes
- May cause skin irritation, burning, or redness
- DMSO may carry substances on the skin surface into the body

Stop use and ask a doctor if

- Condition worsens
- Symptoms persist for more than 7 days

Keep out of reach of children.

If swallowed, get medical help or contact a Poison Control Center right away.

Directions:

- Cleanse and dry the affected area
- Apply a thin layer over the affected area twice daily (morning and evening)
- Wash hands after each use
- Children under 12 years: ask a doctor

Inactive ingredients:

- Water (Aqua)
- Dimethyl Sulfoxide (DMSO)
- Aloe Barbadensis Leaf Juice
- Magnesium Chloride
- Methylsulfonylmethane (MSM)
- Arnica Montana Flower Extract
- Glycerin
- Butyrospermum Parkii (Shea) Butter
- Phenoxyethanol
- Ethylhexylglycerin

OTHER SAFETY INFORMATION

- Store at 20–25°C (68–77°F)
- Protect from excessive heat and direct sunlight
- For external use only

OTHER SAFETY INFORMATION

- Store at 20–25°C (68–77°F)
- Protect from excessive heat and direct sunlight
- For external use only

Questions or comments?

- support@tagridstore.com
- Distributed by TAGRID LLC
- San Francisco, CA, USA 94131
- Website: tagridstore.com